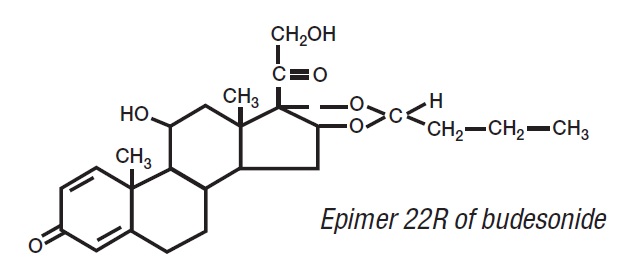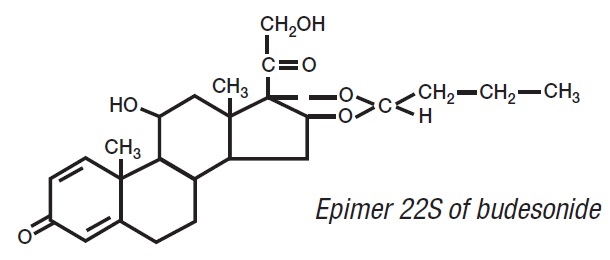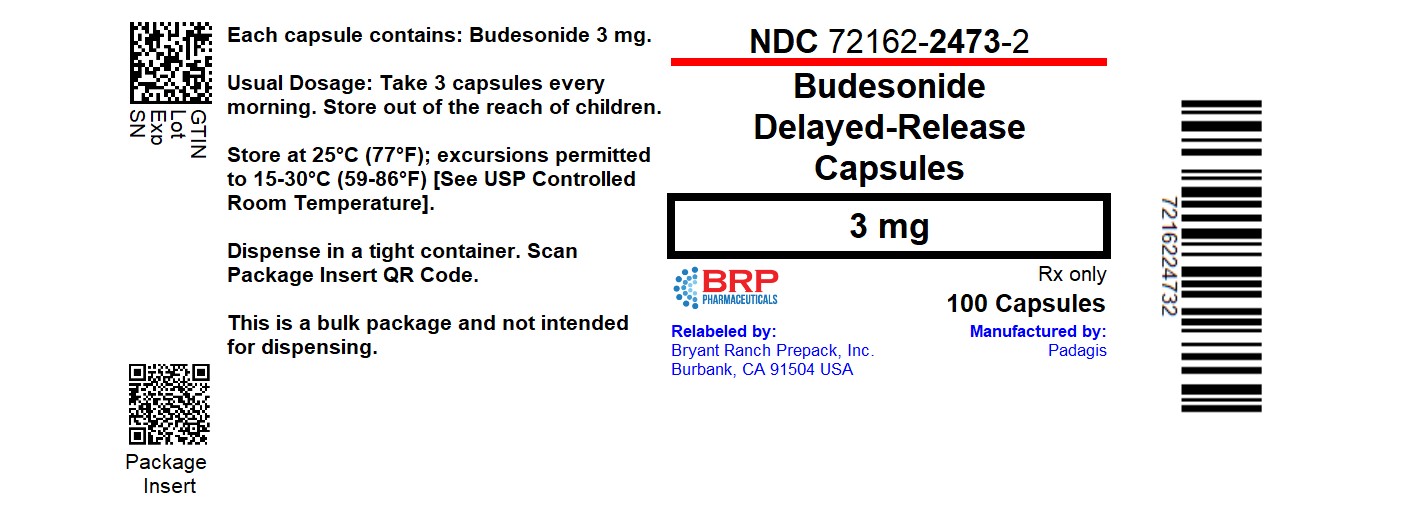 DRUG LABEL: budesonide
NDC: 72162-2473 | Form: CAPSULE
Manufacturer: Bryant Ranch Prepack
Category: prescription | Type: HUMAN PRESCRIPTION DRUG LABEL
Date: 20260217

ACTIVE INGREDIENTS: BUDESONIDE 3 mg/1 1
INACTIVE INGREDIENTS: ETHYLCELLULOSE, UNSPECIFIED; ACETYLTRIBUTYL CITRATE; METHACRYLIC ACID AND ETHYL ACRYLATE COPOLYMER; TRIETHYL CITRATE; POLYSORBATE 80; TALC; GELATIN, UNSPECIFIED; FERRIC OXIDE RED; TITANIUM DIOXIDE

HIGHLIGHTS OF PRESCRIBING INFORMATION

These highlights do not include all the information needed to use BUDESONIDE DELAYED-RELEASE CAPSULESsafely and effectively. See full prescribing information for BUDESONIDE DELAYED-RELEASE CAPSULES.
BUDESONIDE delayed-release capsules, for oral use
Initial U.S. Approval: 1997

RECENT MAJOR CHANGES

Warnings and Precautions
Immunosuppression and Increased Risk of Infection (5.3) | 06/2024
Kaposi's Sarcoma (5.4) | 06/2024

1 INDICATIONS AND USAGE

Budesonide delayed-release capsules are a corticosteroid indicated for:

- Treatment of mild to moderate active Crohn’s disease involving the ileum and/or the ascending colon, in patients 8 years and older. (1.1)
- Maintenance of clinical remission of mild to moderate Crohn’s disease involving the ileum and/or the ascending colon for up to 3 months in adults. (1.2)

2 DOSAGE AND ADMINISTRATION

Administration Instructions(2.1):

- Take once daily in the morning.
- Swallow whole. Do not chew or crush.
- For patients unable to swallow an intact capsule, open the capsules and empty the granules onto one tablespoonful of applesauce. Mix and consume the entire contents within 30 minutes. Do not chew or crush. Follow with 8 ounces of water.
- Avoid consumption of grapefruit juice for the duration of therapy.

Recommended Dosage:

Mild to moderate active Crohn’s disease (2.2):

- Adults: 9 mg once daily for up to 8 weeks; repeat 8 week treatment courses for recurring episodes of active disease.
- Pediatrics 8 to 17 years who weigh more than 25 kg: 9 mg once daily for up to 8 weeks, followed by 6 mg once daily in the morning for 2 weeks.

Maintenance of clinical remission of mild to moderate Crohn’s disease (2.3):

- Adults: 6 mg once daily for up to 3 months; taper to complete cessation after 3 months. Continued treatment for more than 3 months has not been shown to provide substantial clinical benefit.
- When switching from oral prednisolone, begin tapering prednisolone concomitantly with initiating budesonide delayed-release capsules.

Hepatic Impairment:

- Consider reducing the dosage to 3 mg once daily in adult patients with moderate hepatic impairment (Child-Pugh Class B). (2.4, 5.1, 8.6)

3 DOSAGE FORMS AND STRENGTHS

Delayed-release Capsules: 3 mg (3)

4 CONTRAINDICATIONS

Hypersensitivity to budesonide or any of the ingredients in budesonide delayed-release capsules. (4)

5 WARNINGS AND PRECAUTIONS

- Hypercorticism and Adrenal Axis Suppression: May occur with treatment; monitor for signs and symptoms; pediatrics and patients with hepatic impairment may be at increased risk. (2.4, 5.1, 8.4, 8.6)
- Symptoms of Steroid Withdrawal in Patients Transferred from Other Systemic Corticosteroids: Taper slowly from corticosteroids with high systemic effects; monitor for withdrawal symptoms and unmasking of allergies (rhinitis, eczema). (5.2)
- Immunosuppression and Increased Risk of Infection: Increased risk of viral, bacterial, fungal, protozoal and helminthic infections, including potentially fatal varicella and measles infection. Monitor patients for new or worsening infection and consider drug discontinuation. Avoid use in patients with fungal infections, Strongyloides infestation, cerebral malaria and ocular herpes simplex. Screen for hepatitis B infection. (5.3)
- Karposi’s Sarcoma: Reported to occur in patients receiving corticosteroid therapy, most often for chronic conditions. (5.4)
- Other Corticosteroid Effects: Monitor patients with concomitant conditions where corticosteroids may have unwanted effects (e.g., hypertension, diabetes mellitus). (5.5)

6 ADVERSE REACTIONS

Most common adverse reactions (≥5%) in adults are: headache, respiratory infection, nausea, back pain, dyspepsia, dizziness, abdominal pain, flatulence, vomiting, fatigue, and pain. (6.1)

To report SUSPECTED ADVERSE REACTIONS, contact Padagis®at 1-866-634-9120 or FDA at 1-800-FDA-1088 or www.fda.gov/medwatch.

7 DRUG INTERACTIONS

CYP3A4 Inhibitors (e.g., ketoconazole, grapefruit juice): Can increase systemic budesonide concentrations: avoid use. (2.1, 7.1)

8 USE IN SPECIFIC POPULATIONS

Pregnancy: Based on animal data, may cause fetal harm. (8.1)

FULL PRESCRIBING INFORMATION

1 INDICATIONS AND USAGE

1.1 Treatment of Mild to Moderate Active Crohn’s Disease

Budesonide delayed-release capsules are indicated for the treatment of mild to moderate active Crohn's disease involving the ileum and/or the ascending colon in patients 8 years of age and older.

1.2 Maintenance of Clinical Remission of Mild to Moderate Crohn’s Disease

Budesonide delayed-release capsules are indicated for the maintenance of clinical remission of mild to moderate Crohn’s disease involving the ileum and/or the ascending colon for up to 3 months in adults.

2 DOSAGE AND ADMINISTRATION

2.1 Administration Instructions

- Take budesonide delayed-release capsules once daily in the morning.
- Swallow budesonide delayed-release capsules whole. Do not chew or crush.
- For patients unable to swallow an intact capsule, budesonide delayed-release capsules can be opened and administered as follows:
- Place one tablespoonful of applesauce into a clean container (e.g., empty bowl). The applesauce used should not be hot and should be soft enough to be swallowed without chewing.
- Open the capsule(s).
- Carefully empty all the granules inside the capsule(s) on the applesauce.
- Mix the granules with the applesauce.
- Consume the entire contents within 30 minutes of mixing. Do not chew or crush the granules. Do not save the applesauce and granules for future use.
- Follow the applesauce and granules immediately with a glass (8 ounces) of cool water to ensure complete swallowing of the granules.
- Avoid consumption of grapefruit juice for the duration of budesonide delayed-release capsule therapy [see Drug Interactions (7.1)].

2.2 Treatment of Mild to Moderate Active Crohn’s Disease

The recommended dosage of budesonide delayed-release capsules is:

Adults: 9 mg orally once daily for up to 8 weeks. Repeated 8 week courses of budesonide delayed-release capsules can be given for recurring episodes of active disease.

Pediatric patients 8 to 17 years who weigh more than 25 kg: 9 mg orally once daily for up to 8 weeks, followed by 6 mg once daily for 2 weeks.

2.3 Maintenance of Clinical Remission of Mild to Moderate Crohn’s Disease

The recommended dosage in adults, following an 8 week course(s) of treatment for active disease and once the patient’s symptoms are controlled (CDAI less than 150), is budesonide delayed-release capsules 6 mg orally once daily for maintenance of clinical remission up to 3 months. If symptom control is still maintained at 3 months an attempt to taper to complete cessation is recommended. Continued treatment with budesonide delayed-release capsules 6 mg for more than 3 months has not been shown to provide substantial clinical benefit.

Patients with mild to moderate active Crohn’s disease involving the ileum and/or ascending colon have been switched from oral prednisolone to budesonide delayed-release capsules with no reported episodes of adrenal insufficiency. Since prednisolone should not be stopped abruptly, tapering should begin concomitantly with initiating budesonide delayed-release capsules treatment.

2.4 Dosage Adjustment in Adult Patients with Hepatic Impairment

Consider reducing the dosage of budesonide delayed-release capsules to 3 mg once daily for adult patients with moderate hepatic impairment (Child-Pugh Class B). Avoid use in patients with severe hepatic impairment (Child-Pugh Class C) [see Warnings and Precautions (5.1), Use in Specific Populations (8.6)].

3 DOSAGE FORMS AND STRENGTHS

Delayed-Release Capsules: 3 mg hard gelatin capsules with an opaque light grey body and an opaque pink cap, coded with ENTOCORT EC 3 mg.

4 CONTRAINDICATIONS

Budesonide delayed-release capsules are contraindicated in patients with hypersensitivity to budesonide or any of the ingredients of budesonide delayed-release capsules. Serious hypersensitivity reactions, including anaphylaxis have occurred [see Adverse Reactions (6.2)].

5 WARNINGS AND PRECAUTIONS

5.1 Hypercorticism and Adrenal Axis Suppression

Systemic effects such as hypercorticism and adrenal axis suppression may occur with use of corticosteroids, including budesonide delayed-release capsules [see Adverse Reactions (6.1), Clinical Pharmacology (12.2)]. Pediatric patients with Crohn’s disease have a slightly higher systemic exposure of budesonide and increased cortisol suppression than adults with Crohn’s disease [see Use in Specific Populations (8.4), Clinical Pharmacology (12.2)]. Monitor patients for signs and symptoms of hypercorticism and adrenal axis suppression during treatment with budesonide delayed-release capsules.

Patients with moderate to severe hepatic impairment (Child-Pugh Class B and C respectively) could be at an increased risk of hypercorticism and adrenal axis suppression due to an increased systemic exposure of oral budesonide. Avoid use in patients with severe hepatic impairment (Child-Pugh Class C). Monitor for increased signs and/or symptoms of hypercorticism and consider reducing the dosage in patients with moderate hepatic impairment (Child-Pugh Class B) [see Dosage and Administration (2.4), Use in Specific Populations (8.6), Clinical Pharmacology (12.3)].

Corticosteroids, including budesonide delayed-release capsules, can reduce the response of the hypothalamus-pituitary-adrenal (HPA) axis to stress. In situations where patients are subject to surgery or other stress situations, supplementation with a systemic corticosteroid is recommended.

5.2 Symptoms of Steroid Withdrawal in Patients Transferred from Other Systemic Corticosteroids

Monitor patients who are transferred from corticosteroid treatment with high systemic effects to corticosteroids with lower systemic availability, such as budesonide delayed-release capsules, since symptoms attributed to withdrawal of steroid therapy, including those of acute adrenal axis suppression or benign intracranial hypertension, may develop. Adrenocortical function monitoring may be required in these patients and the dose of corticosteroid treatment with high systemic effects should be reduced cautiously.

Replacement of systemic corticosteroids with budesonide delayed-release capsules may unmask allergies (e.g., rhinitis and eczema), which were previously controlled by the systemic drug.

5.3 Immunosuppression and Increased Risk of Infection

Corticosteroids, including budesonide delayed-release capsules, suppress the immune system and increase the risk of infection with any pathogen, including viral, bacterial, fungal, protozoan, or helminthic pathogens. Corticosteroids can:

- Reduce resistance to new infections
- Exacerbate existing infections
- Increase the risk of disseminated infections
- Increase the risk of reactivation or exacerbation of latent infections
- Mask some signs of infection

Corticosteroid-associated infections can be mild but can be severe and at times fatal. The rate of infectious complications increases with increasing corticosteroid dosages.

Monitor patients for the development of infection and consider discontinuation of budesonide delayed-release capsules if the patient develops an infection while on treatment.

Tuberculosis

If budesonide delayed-release capsules is used in patients with latent tuberculosis or tuberculin reactivity, reactivation of tuberculosis may occur. Closely monitor such patients for reactivation. During prolonged budesonide delayed-release capsules therapy, patients with latent tuberculosis or tuberculin reactivity should receive chemoprophylaxis.

Varicella Zoster and Measles Viral Infections

Varicella and measles can have a serious or even fatal course in non-immune pediatric and adult patients taking corticosteroids, including budesonide delayed-release capsules. In corticosteroid-treated patients who have not had these diseases or are non-immune, particular care should be taken to avoid exposure to varicella and measles:

- If an budesonide delayed-release capsules-treated patient is exposed to varicella, prophylaxis with varicella zoster immune globulin may be indicated. If varicella develops, treatment with antiviral agents may be considered.
- If an budesonide delayed-release capsules-treated patient is exposed to measles, prophylaxis with immunoglobulin may be indicated.

Hepatitis B Virus Reactivation

Hepatitis B virus reactivation can occur in patients who are hepatitis B carriers treated with immunosuppressive dosages of corticosteroids, including budesonide delayed-release capsules. Reactivation can also occur infrequently in corticosteroid-treated patients who appear to have resolved hepatitis B infection.

Screen patients for hepatitis B infection before initiating immunosuppressive (e.g., prolonged) treatment with budesonide delayed-release capsules. For patients who show evidence of hepatitis B infection, recommend consultation with physicians with expertise in managing hepatitis B regarding monitoring and consideration for hepatitis B antiviral therapy.

Fungal Infections

Corticosteroids, including budesonide delayed-release capsules, may exacerbate systemic fungal infections; therefore, avoid budesonide delayed-release capsules use in the presence of such infections. For patients on chronic budesonide delayed-release capsules therapy who develop systemic fungal infections, budesonide delayed-release capsules withdrawal or dosage reduction is recommended.

Amebiasis

Corticosteroids, including budesonide delayed-release capsules, may activate latent amebiasis. Therefore, it is recommended that latent amebiasis or active amebiasis be ruled out before initiating budesonide delayed-release capsules in patients who have spent time in the tropics or patients with unexplained diarrhea.

StrongyloidesInfestation

Avoid budesonide delayed-release capsules in patients with known or suspected Strongyloides(threadworm) infection. Corticosteroid-induced immunosuppression may lead to Strongyloidessuperinfection and dissemination with widespread larval migration, often accompanied by severe enterocolitis and potentially fatal gram-negative septicemia.

Cerebral Malaria

Avoid corticosteroids, including budesonide delayed-release capsules, in patients with cerebral malaria.

Ocular Herpes Simplex

Avoid corticosteroids, including budesonide delayed-release capsules, in patients with active ocular herpes simplex

5.4 Kaposi’s Sarcoma

Kaposi’s sarcoma has been reported to occur in patients receiving corticosteroid therapy, most often for chronic conditions. Discontinuation of corticosteroids may result in clinical improvement of Kaposi’s sarcoma.

5.5 Other Corticosteroid Effects

Monitor patients with hypertension, diabetes mellitus, osteoporosis, peptic ulcer, glaucoma or cataracts, or with a family history of diabetes or glaucoma, or with any other condition where corticosteroids may have unwanted effects.

6 ADVERSE REACTIONS

The following clinically significant adverse reactions are described elsewhere in labeling:

- Hypercorticism and adrenal axis suppression [see Warnings and Precautions (5.1)]
- Symptoms of steroid withdrawal in those patients transferred from other systemic corticosteroids [see Warnings and Precautions (5.2)]
- Immunosuppression and increased risk of infection [see Warnings and Precautions (5.3)]
- Kaposi’s sarcoma [see Warnings and Precautions (5.4)]
- Other corticosteroid effects [see Warnings and Precautions (5.5)]

6.1 Clinical Trials Experience

Because clinical trials are conducted under widely varying conditions, adverse reaction rates observed in the clinical trials of a drug cannot be directly compared to rates in the clinical trials of another drug and may not reflect the rates observed in practice.

Adults

The data described below reflect exposure to budesonide delayed-release capsules in 520 patients with Crohn’s disease, including 520 exposed to 9 mg per day (total daily dose) for 8 weeks and 145 exposed to 6 mg per day for one year in placebo controlled clinical trials. Of the 520 patients, 38% were males and the age range was 17 to 74 years.

Treatment of Mild to Moderate Active Crohn’s Disease

The safety of budesonide delayed-release capsules was evaluated in 651 adult patients in five clinical trials of 8 weeks duration in patients with active mild to moderate Crohn’s disease. The most common adverse reactions, occurring in greater than or equal to 5% of the patients, are listed in Table 1.

Table 1: Common Adverse Reactions^1in 8-Week Treatment Clinical Trials

Adverse Reaction | Budesonide Delayed-Release Capsules 9 mg; n=520; Number (%) | Placebo; n=107; Number (%) | Prednisolone^2; 40 mg; n=145; Number (%) | Comparator^3; n=88; Number (%)
Headache | 107 (21) | 19 (18) | 31 (21) | 11 (13)
Respiratory Infection | 55 (11) | 7 (7) | 20 (14) | 5 (6)
Nausea | 57 (11) | 10 (9) | 18 (12) | 7 (8)
Back Pain | 36 (7) | 10 (9) | 17 (12) | 5 (6)
Dyspepsia | 31 (6) | 4 (4) | 17 (12) | 3 (3)
Dizziness | 38 (7) | 5 (5) | 18 (12) | 5 (6)
Abdominal Pain | 32 (6) | 18 (17) | 6 (4) | 10 (11)
Flatulence | 30 (6) | 6 (6) | 12 (8) | 5 (6)
Vomiting | 29 (6) | 6 (6) | 6 (4) | 6 (7)
Fatigue | 25 (5) | 8 (7) | 11 (8) | 0 (0)
Pain | 24 (5) | 8 (7) | 17 (12) | 2 (2)

^1.Occurring in greater than or equal to 5% of the patients in any treated group.

^2.Prednisolone tapering scheme: either 40 mg in week 1 to 2, thereafter tapering with 5 mg per week; or 40 mg in week 1 to 2, 30 mg in week 3 to 4, thereafter tapering with 5 mg per week.

^3.This drug is not approved for the treatment of Crohn’s disease in the United States.

The incidence of signs and symptoms of hypercorticism reported by active questioning of patients in 4 of the 5 short-term clinical trials are displayed in Table 2.

Table 2: Summary and Incidence of Signs/Symptoms of Hypercorticism in 8-Week Treatment Clinical Trials

Signs/Symptom | Budesonide Delayed-Release Capsules 9 mg; n=427; Number (%) | Placebo; n=107; Number (%) | Prednisolone^1; 40 mg; n=145; Number (%)
Total | 145 (34%) | 29 (27%) | 69 (48%)
Acne | 63 (15) | 14 (13) | 33 (23)^2
Bruising Easily | 63 (15) | 12 (11) | 13 (9)
Moon Face | 46 (11) | 4 (4) | 53 (37)^2
Swollen Ankles | 32 (7) | 6 (6) | 13 (9)
Hirsutism^3 | 22 (5) | 2 (2) | 5 (3)
Buffalo Hump | 6 (1) | 2 (2) | 5 (3)
Skin Striae | 4 (1) | 2 (2) | 0 (0)

^1.Prednisolone tapering scheme: either 40 mg in week 1-2, thereafter tapering with 5 mg/week; or 40 mg in week 1 to 2, 30 mg in week 3 to 4, thereafter tapering with 5 mg/week.

^2.Statistically significantly different from budesonide delayed-release capsules 9 mg

^3.Including hair growth increased, local and hair growth increased, general

Maintenance of Clinical Remission of Mild to Moderate Crohn’s Disease

The safety of budesonide delayed-release capsules was evaluated in 233 adult patients in four long-term clinical trials (52 weeks) of maintenance of clinical remission in patients with mild to moderate Crohn’s disease. A total of 145 patients were treated with budesonide delayed-release capsules 6 mg once daily.

The adverse reaction profile of budesonide delayed-release capsules 6 mg once daily in maintenance of Crohn’s disease was similar to that of short-term treatment with budesonide delayed-release capsules 9 mg once daily in active Crohn’s disease. In the long-term clinical trials, the following adverse reactions occurred in greater than or equal to 5% and are not listed in Table 1: diarrhea (10%); sinusitis (8%); infection viral (6%); and arthralgia (5%).

Signs/symptoms of hypercorticism reported by active questioning of patients in the long-term maintenance clinical trials are displayed in Table 3.

Table 3: Summary and Incidence of Signs/Symptoms of Hypercorticism in Long-Term Clinical Trials

Signs/Symptom | Budesonide Delayed-Release Capsules 3 mg; n=88; Number (%) | Budesonide Delayed-Release Capsules 6 mg; n=145; Number (%) | Placebo; n=143; Number (%)
Bruising Easily | 4 (5) | 15 (10) | 5 (4)
Acne | 4 (5) | 14 (10) | 3 (2)
Moon Face | 3 (3) | 6 (4) | 0
Hirsutism | 2 (2) | 5 (3) | 1(1)
Swollen Ankles | 2 (2) | 3 (2) | 3 (2)
Buffalo Hump | 1 (1) | 1 (1) | 0
Skin Striae | 2 (2) | 0 | 0

The incidence of signs/symptoms of hypercorticism as described above in long-term maintenance clinical trials was similar to that seen in the short-term treatment clinical trials.

Less Common Adverse Reactions in Treatment and Maintenance Clinical Trials

Less common adverse reactions (less than 5%), occurring in adult patients treated with budesonide delayed-release capsules 9 mg (total daily dose) in short-term treatment clinical studies and/or budesonide delayed-release capsules 6 mg (total daily dose) in long-term maintenance clinical trials, with an incidence are listed below by system organ class:

Cardiac disorders:palpitation, tachycardia

Eye disorders:eye abnormality, vision abnormal

General disorders and administration site conditions:asthenia, chest pain, dependent edema, face edema, flu-like disorder, malaise, fever

Gastrointestinal disorders:anus disorder, enteritis, epigastric pain, gastrointestinal fistula, glossitis, hemorrhoids, intestinal obstruction, tongue edema, tooth disorder

Infections and infestations:Ear infection - not otherwise specified, bronchitis, abscess, rhinitis, urinary tract infection, thrush

Investigations:weight increased

Metabolism and nutrition disorders:appetite increased

Musculoskeletal and connective tissue disorders:arthritis, cramps, myalgia

Nervous system disorders:hyperkinesia, paresthesia, tremor, vertigo, somnolence, amnesia

Psychiatric disorders:agitation, confusion, insomnia, nervousness, sleep disorder

Renal and urinary disorders:dysuria, micturition frequency, nocturia

Reproductive system and breast disorders:intermenstrual bleeding, menstrual disorder

Respiratory, thoracic and mediastinal disorders:dyspnea, pharynx disorder

Skin and subcutaneous tissue disorders:alopecia, dermatitis, eczema, skin disorder, sweating increased, purpura

Vascular disorders:flushing, hypertension

Bone Mineral Density

A randomized, open, parallel-group multicenter safety clinical trial specifically compared the effect of budesonide delayed-release capsules (less than 9 mg per day) and prednisolone (less than 40 mg per day) on bone mineral density over 2 years when used at doses adjusted to disease severity. Bone mineral density decreased significantly less with budesonide delayed-release capsules than with prednisolone in steroid-naïve patients, whereas no difference could be detected between treatment groups for steroid-dependent patients and previous steroid users. The incidence of symptoms associated with hypercorticism was significantly higher with prednisolone treatment.

Clinical Laboratory Test Findings

The following potentially clinically significant laboratory changes in clinical trials, irrespective of relationship to budesonide delayed-release capsules, were reported in greater than or equal to 1% of patients: hypokalemia, leukocytosis, anemia, hematuria, pyuria, erythrocyte sedimentation rate increased, alkaline phosphatase increased, atypical neutrophils, c-reactive protein increased and adrenal insufficiency.

Pediatrics -- Treatment of Mild to Moderate Active Crohn’s Disease

Adverse reactions reported in pediatric patients 8 to 17 years of age, who weigh more than 25 kg, were similar to those reactions described above in adult patients.

6.2 Postmarketing Experience

The following adverse reactions have been reported during post-approval use of budesonide delayed-release capsules. Because these reactions are reported voluntarily from a population of uncertain size, it is not always possible to reliably estimate their frequency or establish a causal relationship to drug exposure.

Immune System Disorders:Anaphylactic reactions

Nervous System Disorders:Benign intracranial hypertension

Psychiatric Disorders:Mood swings

7 DRUG INTERACTIONS

7.1 CYP3A4 Inhibitors

Budesonide is a substrate for CYP3A4. Avoid use with CYP3A4 inhibitors. Concomitant oral administration of a strong CYP3A4 inhibitor (ketoconazole) caused an eight-fold increase of the systemic exposure to oral budesonide. Inhibitors of CYP3A4 (e.g., ketoconazole, itraconazole, ritonavir, indinavir, saquinavir, erythromycin, and cyclosporine) can increase systemic budesonide concentrations [see Clinical Pharmacology (12.3)].

Grapefruit Juice

Avoid ingestion of grapefruit juice with budesonide. Intake of grapefruit juice which inhibits CYP3A4 activity with budesonide can increase the systemic exposure for budesonide [see Clinical Pharmacology (12.3)].

8 USE IN SPECIFIC POPULATIONS

8.1 Pregnancy

Risk Summary

Limited published studies report on the use of budesonide in pregnant women; however, the data are insufficient to inform a drug-associated risk for major birth defects and miscarriage. There are clinical considerations [see Clinical Considerations]. In animal reproduction studies with pregnant rats and rabbits, administration of subcutaneous budesonide during organogenesis at doses approximately 0.5 times or 0.05 times, respectively, the maximum recommended human dose, resulted in increased fetal loss, decreased pup weights, and skeletal abnormalities. Maternal toxicity was observed in both rats and rabbits at these dose levels [see Data]. Based on animal data, advise pregnant women of the potential risk to a fetus.

The estimated background risk of major birth defects and miscarriage of the indicated population is unknown. All pregnancies have a background risk of birth defect, loss, or other adverse outcomes. In the U.S. general population, the estimated background risk of major birth defects and miscarriage in clinically recognized pregnancies is 2% to 4% and 15% to 20%, respectively.

Clinical Considerations

Disease-Associated Maternal and/or Embryo/Fetal Risk

Some published epidemiological studies show an association of adverse pregnancy outcomes in women with Crohn’s disease, including preterm birth and low birth weight infants, during periods of increased disease activity (including increased stool frequency and abdominal pain). Pregnant women with Crohn’s disease should be counseled regarding the importance of controlling disease.

Fetal/Neonatal adverse reactions

Hypoadrenalism may occur in infants born of mothers receiving corticosteroids during pregnancy. Infants should be carefully observed for signs of hypoadrenalism, such as poor feeding, irritability, weakness, and vomiting, and managed accordingly [see Warnings and Precautions (5.1)].

Data

Animal Data

Budesonide was teratogenic and embryolethal in rabbits and rats.

In an embryo-fetal development study in pregnant rats dosed subcutaneously with budesonide during the period of organogenesis from gestation days 6-15 there were effects on fetal development and survival at subcutaneous doses up to approximately 500 mcg/kg in rats (approximately 0.5 times the maximum recommended human dose on a body surface area basis). In an embryo-fetal development study in pregnant rabbits dosed during the period of organogenesis from gestation days 6-18, there was an increase in maternal abortion, and effects on fetal development and reduction in litter weights at subcutaneous doses up to approximately 25 mcg/kg in rabbits (approximately 0.05 times the maximum recommended human dose on a body surface area basis). Maternal toxicity, including reduction in body weight gain, was observed at subcutaneous doses of 5 mcg/kg in rabbits (approximately 0.01 times the maximum recommended human dose on a body surface area basis) and 500 mcg/kg in rats (approximately 0.5 times the maximum recommended human dose on a body surface area basis).

In a peri-and post-natal development study, rats dosed subcutaneously with budesonide during the period of Day 15 post coitum to Day 21 postpartum, budesonide had no effects on delivery but did have an effect on growth and development of offspring. In addition, offspring survival was reduced and surviving offspring had decreased mean body weights at birth and during lactation at exposures 0.02 times the MRHD (on a mg/m^2basis at maternal subcutaneous doses of 20 mcg/kg/day and higher). These findings occurred in the presence of maternal toxicity.

8.2 Lactation

Risk Summary

Lactation studies have not been conducted with oral budesonide, including budesonide delayed-release capsules, and no information is available on the effects of the drug on the breastfed infant or the effects of the drug on milk production. One published study reports that budesonide is present in human milk following maternal inhalation of budesonide [see Data]. The developmental and health benefits of breastfeeding should be considered along with the mother’s clinical need for budesonide delayed-release capsules and any potential adverse effects on the breastfed infant from budesonide delayed-release capsules, or from the underlying maternal condition.

Data

One published study reports that budesonide is present in human milk following maternal inhalation of budesonide which resulted in infant doses approximately 0.3% to 1% of the maternal weight-adjusted dosage and a milk/plasma ratio ranging between 0.4 and 0.5. Budesonide plasma concentrations were not detected and no adverse events were noted in the breastfed infants following maternal use of inhaled budesonide. The recommended daily dose of budesonide delayed-release capsules is higher (up to 9 mg daily) compared with inhaled budesonide (up to 800 mcg daily) given to mothers in the above described study.

The maximum budesonide plasma concentration following a 9 mg daily dose (in both single- and repeated-dose pharmacokinetic studies) of oral budesonide is approximately 2.15 to 4.31 ng/mL which is up to 10 times higher than the 0.43 to 0.86 ng/mL for a 800 mcg daily dose of inhaled budesonide at steady state in the above inhalation study. Assuming the coefficient of extrapolation between the inhaled and oral doses is constant across all dose levels, at therapeutic doses of budesonide delayed-release capsules, budesonide exposure to the nursing child may be up to 10 times higher than that by budesonide inhalation.

8.4 Pediatric Use

The safety and effectiveness of budesonide delayed-release capsules have been established in pediatric patients 8 to 17 years of age who weigh more than 25 kg for the treatment of mild to moderate active Crohn’s disease involving the ileum and/or the ascending colon. Use of budesonide delayed-release capsules in this age group is supported by evidence from adequate and well controlled studies of budesonide delayed-release capsules in adults, with additional data from 2 clinical studies in 149 pediatric patients treated up to 8 weeks and one pharmacokinetic study in 8 pediatric patients [see Adverse Reactions (6.1), Clinical Pharmacology (12.3), and Clinical Studies (14.1)].

The observed safety profile of budesonide delayed-release capsules in pediatric patients is consistent with its known safety profile in adults and no new safety concerns were identified [see Adverse Reactions (6.1)].

The safety and effectiveness of budesonide delayed-release capsules have not been established in pediatric patients less than 8 years of age for the treatment of mild to moderate active Crohn’s disease involving the ileum and/or the ascending colon.

The safety and effectiveness of budesonide delayed-release capsules have not been established in pediatric patients for the maintenance of clinical remission of mild to moderate Crohn’s disease. An open-label study to evaluate the safety and tolerability of budesonide delayed-release capsules as maintenance treatment in pediatric patients aged 5 to 17 years was conducted, and did not establish the safety and efficacy of maintenance of clinical remission.

Systemic corticosteroids, including budesonide delayed-release capsules, may cause a reduction of growth velocity in pediatric patients. Pediatric patients with Crohn’s disease have a 17% higher mean systemic exposure and cortisol suppression than adults with Crohn’s disease [see Warnings and Precautions (5.1) and Clinical Pharmacology (12.2)].

8.5 Geriatric Use

Clinical studies of budesonide delayed-release capsules did not include sufficient numbers of patients aged 65 and over to determine whether they respond differently from younger patients. Of the 651 patients treated with budesonide delayed-release capsules in clinical studies, 17 (3%) were greater than or equal to 65 years of age and none were greater than 74 years of age. Other reported clinical experience has not identified differences in responses between the elderly and younger patients. In general, dose selection for an elderly patient should be cautious, usually starting at the low end of the dosing range, reflecting the greater frequency of decreased hepatic, renal, or cardiac function, and of concomitant disease or other drug therapy.

8.6 Hepatic Impairment

Patients with moderate to severe hepatic impairment (Child-Pugh Class B and C, respectively) could be at an increased risk of hypercorticism and adrenal axis suppression due to an increased systemic exposure to budesonide [see Warnings and Precautions (5.1) and Clinical Pharmacology (12.3)]. Avoid use in patients with severe hepatic impairment (Child-Pugh Class C). Monitor for increased signs and/or symptoms of hypercorticism and consider dosage reduction in patients with moderate hepatic impairment (Child-Pugh Class B) [see Dosage and Administration (2.4)]. No dosage adjustment is needed in patients with mild hepatic impairment (Child-Pugh Class A).

10 OVERDOSAGE

Reports of acute toxicity and/or death following overdosage of glucocorticoids are rare. Treatment consists of immediate gastric lavage or emesis followed by supportive and symptomatic therapy.

If corticosteroids are used at excessive doses for prolonged periods, systemic corticosteroid effects such as hypercorticism and adrenal axis suppression may occur. For chronic overdosage in the case of severe disease requiring continuous steroid therapy, the dosage may be reduced temporarily.

Single oral doses of 200 and 400 mg/kg were lethal in female and male mice, respectively. The signs of acute toxicity were decreased motor activity, piloerection and generalized edema.

11 DESCRIPTION

Budesonide, the active ingredient of budesonide delayed-release capsules, is a synthetic corticosteroid. Budesonide is designated chemically as (RS)-11β, 16α, 17,21-tetrahydroxypregna-1,4-diene-3,20-dione cyclic 16,17-acetal with butyraldehyde. Budesonide is provided as a mixture of two epimers (22R and 22S). The empirical formula of budesonide is C25H34O6and its molecular weight is 430.5. Its structural formula is:

Budesonide is a white to off-white, tasteless, odorless powder that is practically insoluble in water and heptane, sparingly soluble in ethanol, and freely soluble in chloroform. Its partition coefficient between octanol and water at pH 5 is 1.6 x 10^3ionic strength 0.01.

Budesonide delayed-release capsules are formulated as hard gelatin capsules filled with enteric-coated granules that dissolve at pH greater than 5.5. Each capsule for oral administration contains 3 mg of micronized budesonide with the following inactive ingredients: ethylcellulose, acetyltributyl citrate, methacrylic acid copolymer type C, triethyl citrate, antifoam M, polysorbate 80, talc, and sugar spheres. The capsule shells have the following inactive ingredients: gelatin, iron oxide, and titanium dioxide.

12 CLINICAL PHARMACOLOGY

12.1 Mechanism of Action

Budesonide is an anti-inflammatory corticosteroid and has a high glucocorticoid effect and a weak mineralocorticoid effect, and the affinity of budesonide to glucocorticoid receptors, which reflects the intrinsic potency of the drug, is about 200-fold that of cortisol and 15-fold that of prednisolone.

12.2 Pharmacodynamics

Treatment with glucocorticoids, including budesonide delayed-release capsules is associated with a suppression of endogenous cortisol concentrations and an impairment of the hypothalamus-pituitary-adrenal (HPA) axis function. There was a positive correlation between the percent (%) reduction of AUC0-24of plasma cortisol and systemic exposure to budesonide both in pediatric and adult patients.

Adults

Plasma cortisol suppression was compared following five days’ administration of budesonide delayed-release capsules and prednisolone in a crossover study in healthy volunteers. The mean decrease in the area under the plasma cortisol concentration-time curve over 24 hour (AUC0-24) was greater (78%) with prednisolone 20 mg per day compared to 45% with budesonide delayed-release capsules 9 mg per day.

Pediatrics

The effect of budesonide on endogenous cortisol concentrations was compared between pediatrics (n=8, aged 9 to 14 years) and adults (n=6) with active Crohn’s disease following administration of budesonide delayed-release capsules 9 mg once daily for 7 days. Compared to baseline values before treatment, the mean decrease in the AUC0-24of cortisol was 64% (±18%) in pediatrics and 50% (±27%) in adults after budesonide delayed-release capsules treatment [see Warnings and Precautions (5.1), Adverse Reactions (6.1) and Use in Specific Populations (8.4)].

The responses to adrenocorticotropin challenge (i.e., ACTH stimulation test) was studied in pediatric patients aged 8 to 17 years, with mild to moderate active Crohn’s disease in randomized, double-blind, active control study [see Clinical Studies (14.1)]. After 8 weeks of treatment with 9 mg once daily budesonide delayed-release capsules or with prednisolone, administered at tapering doses starting from 1 mg/kg, the proportion of patients with normal response to the ACTH challenge was 6% in the budesonide group compared to none in the prednisolone group; the proportion of patients with morning p-cortisol of greater than 5 mcg/dL was 50% in the budesonide group compared to 22% in the prednisolone group. The mean morning p-cortisol was 6.3 mcg/dL in the budesonide group and 2.6 mcg/dL in the prednisolone group (Table 4).

Table 4. Proportion of Pediatric Patients 8 to 17 years old with Peak Endogenous Cortisol Levels (above 18 mcg/dL) after ACTH Stimulation and Normal Response* to ACTH Challenge Following Administration of Budesonide Delayed-Release Capsules or Prednisolone for 8 weeks

 | Budesonide | Prednisolone
Peak plasma cortisol above 18 mcg/dL
At baseline | 91% (20/22) | 91% (21/23)
At week 8 | 25% (4/16) | 0% (0/18)
Normal response* to ACTH challenge
At baseline | 73% (16/22) | 78% (18/23)
At week 8 | 6% (1/16) | 0% (0/18)

*The normal response to ACTH challenge included 3 criteria, as defined in the cosyntropin label:

1) morning cortisol level above 5 mcg/dL; 2) increase in cortisol level by at least 7 mcg/dL above the morning (pre-challenge) level following ACTH challenge; and cortisol level of above 18 mcg/dL following ACTH challenge. Cortisol concentration was measured at 30 min after intravenous or intramuscular injection of 0.25 mg cosyntropin at baseline and at week 8 after treatment.

12.3 Pharmacokinetics

Absorption

Mean oral bioavailability of budesonide ranged from 9% to 21% both in patients and in healthy subjects, demonstrating a high first-pass elimination of the drug.

Budesonide pharmacokinetics were dose-proportional following repeated administration in the dose range of 3 to 15 mg. No accumulation of budesonide was observed following repeated dosing.

Following oral administration of a single dose of 9 mg budesonide delayed-release capsules in healthy subjects under fasting condition, the mean peak plasma concentration (Cmax) and the area under the plasma concentration time curve (AUC) for budesonide were 1.50 ± 0.79 ng/mL and 14.13 ± 7.33 ng•hr/mL, respectively. The time to peak concentration (Tmax) varied between 2 and 8 hours with a median value of 3.5 hours. In a different study, following oral administration of 9 mg budesonide delayed-release capsules for five days in healthy subjects, the mean Cmaxand the steady state AUC for budesonide were 2.28 ± 0.77 ng/mL and 15.93 ± 6.29 ng•hr/mL, respectively.

Following administration of 9 mg budesonide delayed-release capsules once daily in patients with active Crohn’s disease, the mean Cmaxand AUC were 1.7 ± 0.9 ng/mL and 15.1 ± 8.5 ng•hr/mL, respectively. Following administration of budesonide delayed-release capsules, the Tmaxranged in individual patients from 0.5 to 10 hours.

Concomitant administration of a high-fat meal delayed the Tmaxof budesonide by 2.3 hours compared to that under fasted conditions but did not significantly affect the AUC in healthy subjects. The mean Cmaxand AUC of budesonide were similar when single dose of budesonide delayed-release capsules (9 mg) was administered after opening the capsules and sprinkling the granules on applesauce versus as intact capsules in the fasted state (N=24) in healthy subjects. The Tmaxranged from 3 to 10 hours with a median of 4 hours after administration of sprinkled granules on applesauce.

Distribution

The mean volume of distribution (Vss) of budesonide varied between 2.2 and 3.9 L/kg in healthy subjects and in patients. Plasma protein binding was estimated to be 85% to 90% in the concentration range 0.43 to 99.02 ng/mL, independent of gender. The erythrocyte/plasma partition ratio at clinically relevant concentrations was about 0.8.

Elimination

Budesonide had a plasma clearance, 0.9 to 1.8 L/min in healthy adults. Mean plasma clearance after intravenous administration of budesonide in patients with Crohn’s disease was 1.0 L/min. These plasma clearance values approached the estimated liver blood flow, and, accordingly, suggest that budesonide is a high hepatic clearance drug. The plasma elimination half-life, after administration of intravenous doses ranged between 2 and 3.6 hours, and did not differ between healthy adults and patients with Crohn’s disease. The mean ± SD plasma elimination half-life after a single dose of budesonide delayed-release capsules (9 mg) in the fasted state (N=24) in healthy subjects was 6.3 ± 1.6 hours and ranged between 2 and 8 hours.

Metabolism

Following absorption, budesonide is subject to high first pass metabolism (80% to 90%). In vitroexperiments in human liver microsomes demonstrated that budesonide is rapidly and extensively biotransformed, mainly by CYP3A4, to its 2 major metabolites, 6β-hydroxy budesonide and 16α-hydroxy prednisolone. The corticosteroid activity of these metabolites was negligible (less than 1/100) in relation to that of the parent compound. In vivoinvestigations with intravenous doses in healthy subjects were in agreement with the in vitrofindings.

Excretion

Budesonide was excreted in urine and feces in the form of metabolites. After oral as well as intravenous administration of micronized [^3H ]-budesonide, approximately 60% of the recovered radioactivity was found in urine. The major metabolites, including 6β-hydroxy budesonide and 16α-hydroxy prednisolone, are mainly renally excreted, intact or in conjugated forms. No unchanged budesonide was detected in urine.

Specific Populations

Age: Pediatric Population (8 years and older)

The pharmacokinetics of budesonide were investigated in pediatric patients aged 9 to 14 years (n=8) after oral administration of budesonide delayed-release capsules and intravenous administration of budesonide. Following administration of 9 mg budesonide delayed-release capsules once daily for 7 days, the median time to peak plasma concentration of budesonide was 5 hours and the mean peak plasma concentration was 2.58 ± 1.51 ng/mL. The mean AUC was 17.78 ± 5.25 ng•hr/mL and 17% higher than that in adult patients with Crohn’s disease in the same study. The mean absolute oral availability was 9.2% (3 to 17%; n=4) in pediatric patients.

After single dose administration of intravenous budesonide (n=4), the mean volume of distribution (Vss) was 2.2 ± 0.4 L/kg and mean clearance was 0.81 ± 0.2 L/min. The mean elimination half-life was 1.9 hours in pediatric patients. The body-weight normalized clearance in pediatric patients was 20.5 mL/min/kg in comparison to 15.9 mL/min/kg in adult patients after intravenous administration [see Warnings and Precautions (5.1), Use in Specific Population (8.4)].

Hepatic Impairment

In patients with mild (Child-Pugh Class A, n=4) or moderate (Child-Pugh Class B, n=4) hepatic impairment, budesonide 4 mg was administered orally as a single dose. The patients with moderate hepatic impairment had a 3.5-fold higher AUC compared to the healthy subjects with normal hepatic function while the patients with mild hepatic impairment had an approximately 1.4-fold higher AUC. The Cmaxvalues demonstrated similar increases [see Dosage and Administration (2.4), Warnings and Precautions (5.1)]. The increased systemic exposure in patients with mild hepatic impairment was not considered to be clinically relevant. Patients with severe liver impairment (Child-Pugh Class C) were not studied.

Drug Interaction Studies

Budesonide is metabolized via CYP3A4. Potent inhibitors of CYP3A4 can increase the plasma concentrations of budesonide several-fold. Conversely, induction of CYP3A4 potentially could result in the lowering of budesonide plasma concentrations.

Effects of Other Drugs on Budesonide

Ketoconazole

In an open, non-randomized, cross-over study, 6 healthy subjects were given budesonide 10 mg as a single dose, either alone or concomitantly with the last ketoconazole dose of 3 days treatment with ketoconazole 100 mg twice daily. Co-administration of ketoconazole resulted in an eight-fold increase in AUC of budesonide, compared to budesonide alone [see Drug Interactions (7.1)].

Grapefruit Juice

In an open, randomized, cross-over study, 8 healthy subjects were given budesonide delayed-release capsules 3 mg, either alone, or concomitantly with 600 mL concentrated grapefruit juice (which inhibits CYP3A4 activity predominantly in the intestinal mucosa), on the last of 4 daily administrations. Concomitant administration of grapefruit juice resulted in a 2-fold increase of the bioavailability of budesonide compared to budesonide alone [see Drug Interactions (7.1)].

Oral Contraceptives (CYP3A4 Substrates)

In a parallel study, the pharmacokinetics of budesonide were not significantly different between healthy female subjects who received oral contraceptives containing desogestrel 0.15 mg and ethinyl estradiol 30 μg and healthy female subjects who did not receive oral contraceptives. Budesonide 4.5 mg once daily (one-half the recommended dose) for one week did not affect the plasma concentrations of ethinyl estradiol, a CYP3A4 substrate. The effect of budesonide 9 mg once daily on the plasma concentrations of ethinyl estradiol was not studied.

Omeprazole

In a study in 11 healthy subjects, performed in a double-blind, randomized, placebo controlled manner, the effect of 5 to 6 days treatment with omeprazole 20 mg once daily on the pharmacokinetics of budesonide administered as budesonide delayed-release capsules 9 mg as a single dose was investigated. Omeprazole 20 mg once daily did not affect the absorption or pharmacokinetics of budesonide.

Cimetidine

In an open, non-randomized, cross-over study, the potential effect of cimetidine on the pharmacokinetics of budesonide was studied. Six healthy subjects received cimetidine 1 gram daily (200 mg with meals and 400 mg at night) for 2 separate 3-day periods. Budesonide 4 mg was administered either alone or on the last day of one of the cimetidine treatment periods. Co-administration of cimetidine resulted in a 52% and 31% increase in the budesonide peak plasma concentration and the AUC of budesonide, respectively.

13 NONCLINICAL TOXICOLOGY

13.1 Carcinogenesis, Mutagenesis, Impairment of Fertility

Carcinogenicity studies with budesonide were conducted in rats and mice. In a two-year study in Sprague-Dawley rats, budesonide caused a statistically significant increase in the incidence of gliomas in male rats at an oral dose of 50 mcg/kg (approximately 0.05 times the maximum recommended human dose on a body surface area basis). In addition, there were increased incidences of primary hepatocellular tumors in male rats at 25 mcg/kg (approximately 0.023 times the maximum recommended human dose on a body surface area basis) and above. No tumorigenicity was seen in female rats at oral doses up to 50 mcg/kg (approximately 0.05 times the maximum recommended human dose on a body surface area basis). In an additional two-year study in male Sprague-Dawley rats, budesonide caused no gliomas at an oral dose of 50 mcg/kg (approximately 0.05 times the maximum recommended human dose on a body surface area basis). However, it caused a statistically significant increase in the incidence of hepatocellular tumors at an oral dose of 50 mcg/kg (approximately 0.05 times the maximum recommended human dose on a body surface area basis). The concurrent reference corticosteroids (prednisolone and triamcinolone acetonide) showed similar findings. In a 91-week study in mice, budesonide caused no treatment-related carcinogenicity at oral doses up to 200 mcg/kg (approximately 0.1 times the maximum recommended human dose on a body surface area basis).

Budesonide was not genotoxic in the Ames test, the mouse lymphoma cell forward gene mutation (TK+/-) test, the human lymphocyte chromosome aberration test, the Drosophila melanogastersex-linked recessive lethality test, the rat hepatocyte UDS test and the mouse micronucleus test.

In rats, budesonide had no effect on fertility at subcutaneous doses up to 80 mcg/kg (approximately 0.07 times the maximum recommended human dose on a body surface area basis). However, it caused a decrease in prenatal viability and viability in pups at birth and during lactation, along with a decrease in maternal body-weight gain, at subcutaneous doses of 20 mcg/kg (approximately 0.02 times the maximum recommended human dose on a body surface area basis) and above. No such effects were noted at 5 mcg/kg (approximately 0.005 times the maximum recommended human dose on a body surface area basis).

14 CLINICAL STUDIES

14.1 Treatment of Mild to Moderate Active Crohn’s Disease

Adults

The efficacy of budesonide delayed-release capsules were evaluated in 994 patients with mild to moderate active Crohn’s disease of the ileum and/or ascending colon in 5 randomized and double-blind studies of 8 weeks duration. The study patients ranged in age from 17 to 85 (mean 35), 40% were male and 97% were white. The Crohn’s Disease Activity Index (CDAI) was the main clinical assessment used for determining efficacy in these 5 studies.^1The CDAI is a validated index based on subjective aspects rated by the patient (frequency of liquid or very soft stools, abdominal pain rating and general well-being) and objective observations (number of extraintestinal symptoms, need for antidiarrheal drugs, presence of abdominal mass, body weight and hematocrit). Clinical improvement, defined as a CDAI score of less than or equal to 150 assessed after 8 weeks of treatment, was the primary efficacy variable in these 5 comparative efficacy studies of budesonide delayed-release capsules. Safety assessments in these studies included monitoring of adverse reactions. A checklist of potential symptoms of hypercorticism was used.

One study (Study 1) compared the efficacy of budesonide delayed-release capsules 9 mg daily in the morning to a comparator. At baseline, the median CDAI was 272. Budesonide delayed-release capsules 9 mg daily resulted in a significantly higher clinical improvement rate at Week 8 than the comparator. See Table 5.

Table 5: Clinical Improvement Rates (CDAI less than or equal to 150) After 8 weeks of Treatment

Clinical Study | Budesonide Delayed-release Capsules; 9 mg Daily | Budesonide Delayed-release Capsules; 4.5 mg Twice Daily | Comparator^3 | Placebo | Prednisolone
1 | 62/91 (69%)^1 |  | 37/83 (45%)
2 |  | 31/61 (51%)^2 |  | 13/64 (20%)
3 | 38/79 (48%) | 41/78 (53%) |  | 13/40 (33%)
4 | 35/58 (60%) | 25/60 (42%) |  |  | 35/58 (60%)
5 | 45/86 (52%) |  |  |  | 56/85 (65%)

^1.p=0.0004 compared to comparator.

^2.p=0.001 compared to placebo.

^3.This drug is not approved for the treatment of Crohn’s disease in the United States.

Two placebo-controlled clinical trials (Studies 2 and 3) were conducted. Study 2 involved 258 patients and tested the effects of graded doses of budesonide delayed-release capsules (1.5 mg twice daily, 4.5 mg twice daily, or 7.5 mg twice daily) versus placebo. At baseline, the median CDAI was 290. The 1.5 mg twice daily arm (data not shown) could not be differentiated from placebo. The 4.5 mg twice daily arm was statistically different from placebo (Table 5), while no additional benefit was seen when the daily budesonide delayed-release capsules dose was increased to 15 mg per day (data not shown). Study 3 was a 3-armed parallel group study. The groups were treated with budesonide delayed-release capsules 9 mg once daily, budesonide delayed-release capsules 4.5 mg twice daily and placebo for 8 weeks, followed by a 2-week double-blind taper phase. The median CDAI at baseline was 263. Neither 9 mg daily nor 4.5 mg twice daily budesonide delayed-release capsules dose levels were statistically different from placebo (Table 5). The recommended dosage of budesonide delayed-release capsules for the treatment of mild to moderate active Crohn’s disease involving the ileum and/or the ascending colon in adults is 9 mg once daily in the morning for up to 8 weeks [see Dosage and Administration (2.1)].

Two clinical trials (Studies 4 and 5) compared budesonide delayed-release capsules with oral prednisolone (initial dose 40 mg per day). Study 4 was a 3-armed parallel group study. The groups were treated with budesonide delayed-release capsules 9 mg once daily, budesonide delayed-release capsules 4.5 mg twice daily and prednisolone 40 mg (tapered dose) for 8 weeks, followed by a 4-week double blind taper phase. At baseline, the median CDAI was 277. Equal clinical improvement rates (60%) were seen in the budesonide delayed-release capsules 9 mg daily and the prednisolone groups in Study 4. In Study 5, 13% fewer patients in the budesonide delayed-release capsules group experienced clinical improvement than in the prednisolone group (no statistical difference) (Table 5). The proportion of patients with normal plasma cortisol values (greater than 64.58 ng/mL) was significantly higher in the budesonide delayed-release capsules groups in both trials (60% to 66%) than in the prednisolone groups (26% to 28%) at Week 8.

Pediatrics (8 to 17 Years of Age)

The effectiveness of budesonide delayed-release capsules, in pediatric patients aged 8 to 17 years, who weigh more than 25 kg with mild to moderate active Crohn’s disease (defined as Crohn's Disease Activity Index (CDAI) ≥ 200) involving the ileum and/or the ascending colon, was assessed in one randomized, double-blind, active control study. This study compared budesonide delayed-release capsules 9 mg once daily, with prednisolone, administered at tapering doses starting from 1 mg/kg. Twenty-two (22) patients were treated with budesonide delayed-release capsules capsules and 24 patients were treated with prednisolone. After 8 weeks of treatment, 55% (95% CI: 32%, 77%) of patients treated with budesonide delayed-release capsules reached the endpoint (CDAI ≤150), as compared to 68% (95% CI: 47%, 89%) of patients treated with prednisolone. The average number of liquid or very soft stools per day (assessed over 7 days) decreased from 1.49 at baseline to 0.96 after treatment with budesonide delayed-release capsules and 2.00 at baseline to 0.52 after treatment with prednisolone. The average daily abdominal pain rating (where 0=none, 1=mild, 2=moderate, and 3=severe) decreased from 1.49 at baseline to 0.54 after treatment with budesonide delayed-release capsules and 1.64 at baseline to 0.38 after 8 weeks of treatment with prednisolone.

Use of budesonide delayed-release capsules in this age group is supported by evidence from adequate and well-controlled studies of budesonide delayed-release capsules in adults, and by safety and pharmacokinetic studies performed in pediatric patients.

14.2 Maintenance of Clinical Remission of Mild to Moderate Crohn’s Disease

Adults

The efficacy of budesonide delayed-release capsules for maintenance of clinical remission were evaluated in four double-blind, placebo-controlled, 12-month trials in which 380 patients were randomized and treated once daily with 3 mg or 6 mg budesonide delayed-release capsules or placebo. Patients ranged in age from 18 to 73 (mean 37) years. Sixty percent of the patients were female and 99% were Caucasian. The mean CDAI at entry was 96. Among the four clinical trials, approximately 75% of the patients enrolled had exclusively ileal disease. Colonoscopy was not performed following treatment. Budesonide delayed-release capsules 6 mg per day prolonged the time to relapse, defined as an increase in CDAI of at least 60 units to a total score greater than 150 or withdrawal due to disease deterioration. The median time to relapse in the pooled population of the 4 studies was 154 days for patients taking placebo, and 268 days for patients taking budesonide delayed-release capsules 6 mg per day. Budesonide delayed-release capsules 6 mg per day reduced the proportion of patients with loss of symptom control relative to placebo in the pooled population for the 4 studies at 3 months (28% versus 45% for placebo).

15 REFERENCES

1. Best WR, Becktel JM, Singleton JW, Kern F: Development of a Crohn’s Disease Activity Index, National Cooperative Crohn’s Disease Study. Gastroenterology 1976; 70(3): 439-444.

16 HOW SUPPLIED/STORAGE AND HANDLING

Budesonide 3 mg delayed-release capsules are hard gelatin capsules with an opaque light grey body and an opaque pink cap, coded with ENTOCORT EC 3 mg on the capsule and are supplied as follows:

- NDC 72162-2473-01 Bottles of 100
- NDC 72162-2473-02 Bottles of 100

Store at 25°C (77°F); excursions permitted to 15-30°C (59-86°F) [See USP Controlled Room Temperature].

Keep container tightly closed.

Repackaged/Relabeled by:
Bryant Ranch Prepack
Burbank, CA 91504

17 PATIENT COUNSELING INFORMATION

Advise Patients to read the FDA-Approved patient labeling (Patient Information).

Hypercorticism and Adrenal Axis Suppression

Advise patients that budesonide delayed-release capsules may cause hypercorticism and adrenal axis suppression and to follow a taper schedule, as instructed by their healthcare provider if transferring to budesonide delayed-release capsules from systemic corticosteroids [see Warnings and Precautions (5.1), (5.2)]. Advise patients that replacement of systemic corticosteroids with budesonide delayed-release capsules may unmask allergies (e.g., rhinitis and eczema), which were previously controlled by the systemic drug.

Immunosuppression and Increased Risk of Infection

Advise patients to avoid exposure to people with varicella (chicken pox) or measles. Advise patients inform their healthcare provider if they are exposed to varicella or measles or if they develop a new or worsening infection [see Warnings and Precautions (5.3)].

Kaposi’s Sarcoma

Advise patients that Kaposi’s sarcoma has been reported in patients receiving corticosteroids for chronic conditions and to inform their healthcare provider if they experience signs or symptoms of Kaposi’s sarcoma [see Warnings and Precautions (5.4)].

Pregnancy

Advise female patients that budesonide delayed-release capsules may cause fetal harm and to inform their healthcare provider with a known or suspected pregnancy [see Use in Specific Populations (8.1)].

Administration

1. •Take budesonide delayed-release capsules once daily in the morning.
2. •Swallow budesonide delayed-release capsules whole. Do not chew or crush.
3. •For patients unable to swallow an intact capsule, budesonide delayed-release capsules can be opened and administered as follows:
4. Place one tablespoonful of applesauce into a clean container (e.g., empty bowl). The applesauce used should not be hot and should be soft enough to be swallowed without chewing.
5. Open the capsule(s).
6. Carefully empty all the granules inside the capsule(s) on the applesauce.
7. Mix the granules with the applesauce.
8. Consume the entire contents within 30 minutes of mixing. Do not chew or crush the granules. Do not save the applesauce and granules for future use.
9. Follow the applesauce and granules immediately with a glass (8 ounces) of cool water to ensure complete swallowing of the granules.
10. •Avoid consumption of grapefruit juice for the duration of their budesonide delayed-release capsules therapy [see Drug Interactions (7.1)].

ENTOCORT is a registered trademark of Padagis US LLC. © Padagis LLC 2024

Manufactured for Padagis®
Minneapolis, MN 55427

Rev 06-24
5V000 RC PH8
2204932

PATIENT INFORMATION

Budesonide (bue des' oh nide) delayed-release capsules

Read this Patient Information before you start taking budesonide delayed-release capsules and each time you get a refill. There may be new information. This information does not take the place of talking to your healthcare provider about your medical condition or your treatment.

What are budesonide delayed-release capsules?

Budesonide delayed-release capsules are a prescription corticosteroid medicine used to treat mild to moderate Crohn’s disease that affects part of the small intestine (ileum) and part of the large intestine (ascending colon):

- in people 8 years of age and older with active Crohn’s disease
- in adults to help keep symptoms from coming back for up to 3 months

It is not known if budesonide delayed-release capsules are safe and effective in children under 8 years of age, or in children 8 to 17 years of age who weigh 55 pounds (25 kg) or less, for the treatment of mild to moderate active Crohn’s disease that affects part of the small intestine (ileum) and part of the large intestine (ascending colon).

It is not known if budesonide delayed-release capsules are safe and effective in children to help keep symptoms of mild to moderate Crohn’s disease that affects part of the small intestine (ileum) and part of the large intestine (ascending colon) from coming back.

Who should not take budesonide delayed-release capsules?

Do not take budesonide delayed-release capsules if:

- you are allergic to budesonide or any of the ingredients in budesonide delayed-release capsules. See the end of this leaflet for a complete list of ingredients in budesonide delayed-release capsules.

Before you take budesonide delayed-release capsules tell your healthcare provider if you have any other medical conditions including if you:

- have liver problems.
- are planning to have surgery.
- have chicken pox or measles or have recently been near anyone with chicken pox or measles.
- have an infection, including fungal and threadworm (Strongyloides) infections.
- have diabetes or glaucoma or have a family history of diabetes or glaucoma.
- have cataracts.
- have or had tuberculosis.
- have high blood pressure (hypertension).
- have decreased bone mineral density (osteoporosis).
- have stomach ulcers.
- have malaria of the brain (cerebral malaria).
- are pregnant or plan to become pregnant. Budesonide delayed-release capsules may harm your unborn baby. Talk to your healthcare provider about the possible risk to your unborn baby if you take budesonide delayed-release capsules when you are pregnant. Tell your healthcare provider right away if you become pregnant or think you may be pregnant during your treatment with budesonide delayed-release capsules.
- are breastfeeding or plan to breastfeed. It is not known if budesonide passes into your breast milk or if it will affect your baby. Talk to your healthcare provider about the best way to feed your baby if you take budesonide delayed-release capsules.

Tell your healthcare provider about all the medicines you take,including prescription and over-the-counter medicines, vitamins, and herbal supplements. Budesonide delayed-release capsules and other medicines may affect each other causing side effects.

How should I take budesonide delayed-release capsules?

- Take budesonide delayed-release capsules exactly as your healthcare provider tells you.
- Your healthcare provider will tell you how many budesonide delayed-release capsules to take. Your healthcare provider may change your dose if needed.
- Take budesonide delayed-release capsules 1 time each day in the morning.
- Take budesonide delayed-release capsules whole. Do not chew or crush budesonide delayed-release capsules before swallowing.
- For patients, unable to swallow a whole capsule, budesonide delayed-release capsules can be opened and administered as follows:
- Place 1 tablespoonful of applesauce into a clean container, such as an empty bowl. The applesauce used should not be hot and should be soft enough to be swallowed without chewing.
- Open the capsule. You may need to use more than 1 budesonide delayed-release capsule for the dose prescribed by your healthcare provider.
- Carefully empty all of the granules inside the capsule on the applesauce.
- Stir the granules with the applesauce.
- Swallow the applesauce and granules mixture within 30 minutes after preparing it. Follow the applesauce and granules immediately with a glass (8 ounces) of cool water to help with complete swallowing of the granules.
- Do not chew or crush the granules.
- Do not save the applesauce and granules for later use.
- If you take too many budesonide delayed-release capsules call your healthcare provider right away or go to the nearest hospital emergency room.

What should I avoid while taking budesonide delayed-release capsules?

- Do not drink grapefruit juice during your treatment with budesonide delayed-release capsules. Drinking grapefruit juice can increase the level of budesonide in your blood.

What are the possible side effects of budesonide delayed-release capsules?

Budesonide delayed-release capsules may cause serious side effects, including:

- Effects of having too much corticosteroid medicine in your blood (hypercorticism).Long-time use of budesonide delayed-release capsules can cause you to have too much corticosteroid medicine in your blood. Tell your healthcare provider if you have any of the following signs and symptoms of hypercorticism:

- acne

- thicker or more hair on your body and face

- bruise easily

- a fatty pad or hump between your shoulders (buffalo hump)

- rounding of your face (moon face)

- pink or purple stretch marks on the skin of your abdomen, thighs, breasts and arms

- ankle swelling

- Adrenal suppression.When budesonide delayed-release capsules are taken for a long period of time (chronic use), adrenal suppression can happen. This is a condition in which the adrenal glands do not make enough steroid hormones. Symptoms of adrenal suppression include: tiredness, weakness, nausea and vomiting and low blood pressure. Tell your healthcare provider if you are under stress or have any symptoms of adrenal suppression during treatment with budesonide delayed-release capsules.
- Worsening of allergies.If you take certain other corticosteroid medicines to treat allergies, switching to budesonide delayed-release capsules may cause your allergies to come back. These allergies may include a skin condition called eczema or inflammation inside your nose (rhinitis). Tell your healthcare provider if any of your allergies become worse while taking budesonide delayed-release capsules.
- Decreased ability of your body to fight infections (immunosuppression) and increased risk of infection. Corticosteroid medicines, including budesonide delayed-release capsules, lower the ability of your immune system to fight infections and increase the risk of infections caused by virus, bacteria, fungi, protozoan, or certain parasites. Corticosteroid medicines including budesonide delayed-release capsules can also:
- make current infections worse
- increase the risk of infections spreading (disseminated)
- increase the risk of making infections active again or making infections worse that have not been active (latent)
- hide (mask) some signs of infection
- These infections can be mild, but can be severe and lead to death. Your healthcare provide should check you closely for signs and symptoms of an infection while taking budesonide delayed-release capsules. Tell your healthcare provider right away about any signs or symptoms of a new or worsening infection while taking budesonide delayed-release capsules, including flu-like symptoms such as:

- fever

- cough

- chills
- stomach area (abdominal) pain

stomach area (abdominal) pain

- pain
  feeling tired
- feeling tired

- aches

- nausea and vomiting

- diarrhea

- Tuberculosis: If you have inactive (latent) tuberculosis, your tuberculosis may become active again while taking budesonide delayed-release capsules your healthcare provider should check you closely for signs and symptoms of tuberculosis while taking budesonide delayed-release capsules.
- Chicken pox and measles: People taking corticosteroid medicines, including budesonide delayed-release capsules, who have not had chicken pox or measles, should avoid contact with people who have these diseases. Tell your healthcare provider right away if you come in contact with anyone who has chicken pox or measles.
- Hepatitis B Virus (HBV) reactivation: If you are a carrier of HBV, the virus can become an active infection again while taking budesonide delayed-release capsules. Your healthcare provider will test you for HBV before you start taking budesonide delayed-release capsules.
- Amebiasis: Inactive (latent) amebiasis before you start taking budesonide delayed-release capsules. Your healthcare provider should check you for amebiasis before you start taking budesonide delayed-release capsules in people who have spent time in the tropics or have unexplained diarrhea.
- Kaposi’s Sarcoma. Kaposi’s sarcoma has happened in people who receive corticosteroid therapy, most often for treatment of long-lasting (chronic) conditions.

The most common side effects of budesonide delayed-release capsules in adults include:

- headache

- vomiting

- stomach area (abdominal) pain

- back pain

- infection in your air passages (respiratory infection)

- tiredness

- gas

- indigestion

- nausea

- pain

- dizziness

The most common side effects of budesonide delayed-release capsules in children8 to 17 years of age, who weigh more than 55 pounds (25 kg), are similar to the most common side effects in adults.

Tell your healthcare provider if you have any side effect that bothers you or that does not go away.

These are not all the possible side effects of budesonide delayed-release capsules. For more information, ask your healthcare provider or pharmacist.

Call your doctor for medical advice about side effects. You may report side effects to FDA at 1-800-FDA-1088.

How should I store budesonide delayed-release capsules?

1. •Store budesonide delayed-release capsules at room temperature between 68°F to 77°F (20°C to 25°C).
2. •Keep budesonide delayed-release capsules in a tightly closed container.

Keep budesonide delayed-release capsules and all medicines out of the reach of children.

General information about the safe and effective use of budesonide delayed-release capsules.

Medicines are sometimes prescribed for purposes other than those listed in a Medication Guide or Patient Information leaflet. Do not use budesonide delayed-release capsules for a condition for which it was not prescribed. Do not give budesonide delayed-release capsules to other people, even if they have the same symptoms that you have. It may harm them. You can ask your pharmacist or healthcare provider for information about budesonide delayed-release capsules that is written for health professionals.

What are the ingredients in budesonide delayed-release capsules?

Active ingredient:budesonide

Inactive ingredients:ethylcellulose, acetyltributyl citrate, methacrylic acid copolymer type C, triethyl citrate, antifoam M, polysorbate 80, talc, and sugar spheres. The capsule shell contains: gelatin, iron oxide, and titanium dioxide.

Manufactured for Padagis®
Minneapolis, MN 55427

Rev 06-24
5V000 RC PH8
2204932

For more information, go to www.padagis.com or call 1-866-634-9120.

This Patient Information has been approved by the U.S. Food and Drug Administration.

PACKAGE/LABEL PRINCIPAL DISPLAY PANEL

Budesonide Delayed-Release 3mg Capsules